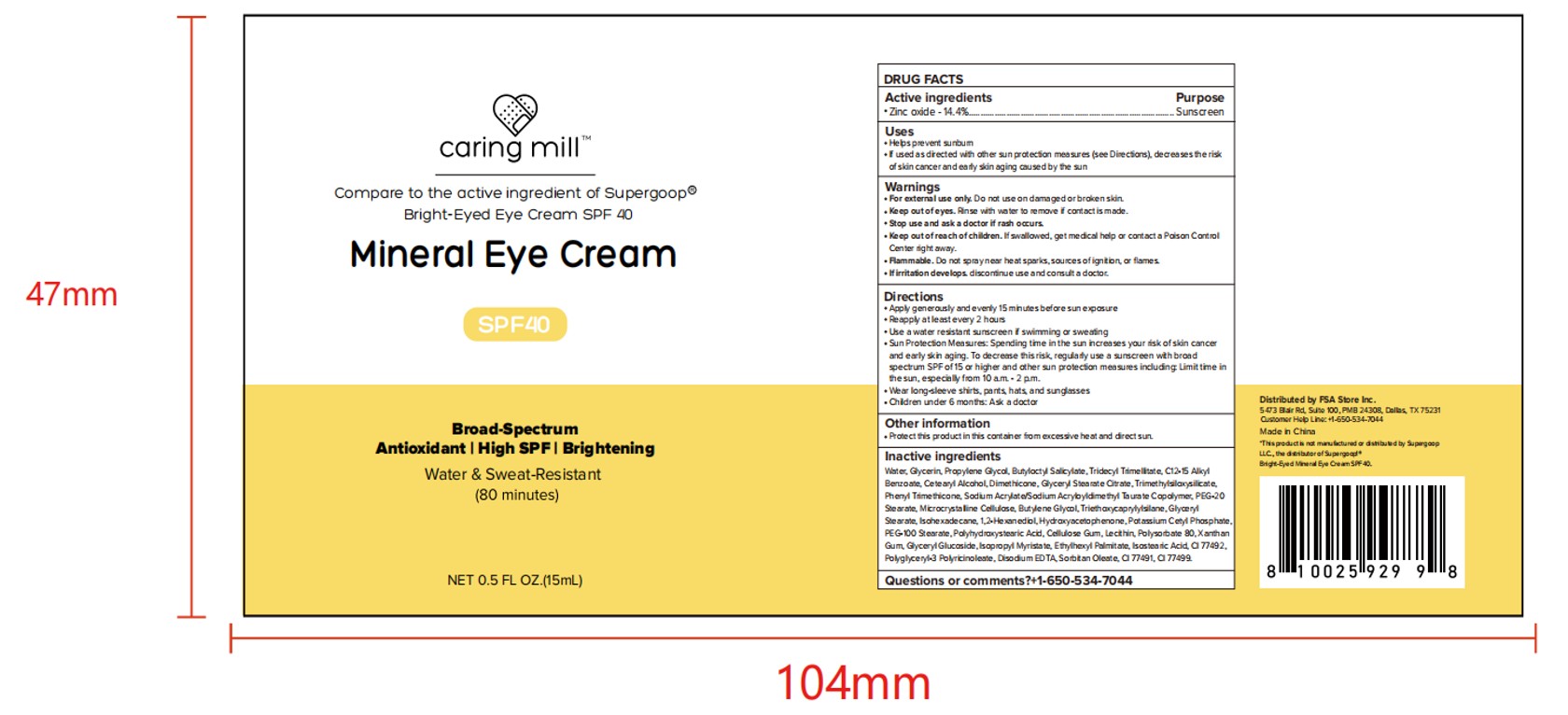 DRUG LABEL: Caring mill Mineral Eye Cream
NDC: 81522-666 | Form: LIQUID
Manufacturer: FSA STORE INC.
Category: otc | Type: HUMAN OTC DRUG LABEL
Date: 20260125

ACTIVE INGREDIENTS: ZINC OXIDE 14.4 g/100 mL
INACTIVE INGREDIENTS: PEG-100 STEARATE; C12-15 ALKYL BENZOATE; EDETATE DISODIUM; CI 77499; GLYCERIN; CETEARYL ALCOHOL; TRIMETHYLSILOXYSILICATE (M/Q 0.8-1.0); ETHYLHEXYL PALMITATE; HYDROXYACETOPHENONE; AQUA; GLYCERYL STEARATE CITRATE; GLYCERYL GLUCOSIDE; CELLULOSE GUM; ISOPROPYL MYRISTATE; ISOHEXADECANE; BUTYLOCTYL SALICYLATE; TRIETHOXYCAPRYLYLSILANE; EGG PHOSPHOLIPIDS; CI 77492; PEG-20 STEARATE; POLYSORBATE 80; SORBITAN OLEATE; ISOSTEARIC ACID; POLYGLYCERYL-3 PENTARICINOLEATE; PHENYL TRIMETHICONE; BUTYLENE GLYCOL; 1,2-HEXANEDIOL; TRIDECYL TRIMELLITATE; CI 77491; PROPYLENE GLYCOL; SODIUM ACRYLATE/SODIUM ACRYLOYLDIMETHYLTAURATE COPOLYMER (4000000 MW); POTASSIUM CETYL PHOSPHATE

ACTIVE INGREDIENT

Zinc oxide

INACTIVE INGREDIENT

WATER
TRIETHOXYCAPRYLYLSILANE
GLYCERIN
PROPYLENE GLYCOL
BUTYLOCTYL SALICYLATE
TRIDECYL TRIMELLITATE
C12-15 ALKYL BENZOATE
SODIUM ACRYLATE/SODIUM ACRYLOYLDIMETHYL TAURATE COPOLYMER
ISOHEXADECANE
POLYSORBATE 80
SORBITAN OLEATE
PEG-20 STEARATE
CETEARYL ALCOHOL
DIMETHICONE
GLYCERYL STEARATE CITRATE
GLYCERYL STEARATE
PEG-100 STEARATE
TRIMETHYLSILOXYSILICATE
CETEARYL ALCOHOL
CELLULOSE GUM
MICROCRYSTALLINE CELLULOSE
PHENYL TRIMETHICONE
POLYHYDROXYSTEARIC ACID
LECITHIN
ISOPROPYL MYRISTATE
ETHYLHEXYL PALMITATE
ISOSTEARIC ACID
POLYGLYCERYL-3 POLYRICINOLEATE
BUTYLENE GLYCOL
1,2-HEXANEDIOL
HYDROXYACETOPHENONE
GLYCERIN
GLYCERYL GLUCOSIDE
POTASSIUM CETYL PHOSPHATE
XANTHAN GUM
DISODIUM EDTA

PURPOSE

Sunscreen

Keep out of reach of children. lf swallowed, get medical help or contact a Poison - ControlCenter right away

WARNINGS

For external use only Do not use on damaged !i or broken skin.
When using this product keep out of eyes.Rise with water to remove.
Stop use and ask a doctor if rash occurs.
Keep out of reach of children. lf swallowed, get medical help or contact a Poison
ControlCenter right away

DOSAGE AND ADMINISTRATION

Apply liberally 15 minutes before sun exposure.
Reapply: at least every 2 hours or after 80 minutes of swimming or sweating.

INDICATIONS AND USAGE

Reapply: at least every 2 hours or after
80 minutes of swimming or sweating. Sun Protection Measures: $pending time in the
sun increases your risk of skin cancer andearly skin aging. To decrease this risk,
regularly use a sunscreen with a Broad Spectrum SPfof 15 or higher and other sun
protection measures including: limit time in the sun, especiallyfrom 10 a.m.-2 pm, and
wear long-sleeved shirts, pants, hats, and sunglasses. Childrenunder 6 months of age
ask a doctor.